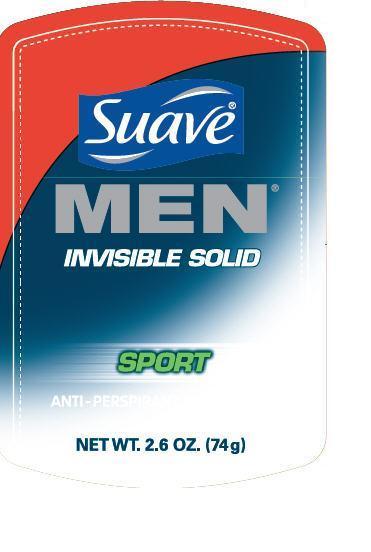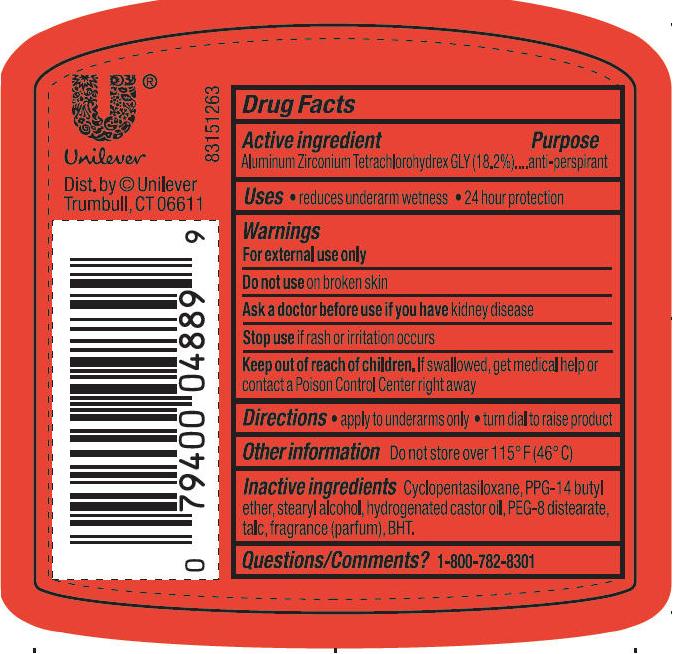 DRUG LABEL: Suave
NDC: 64942-1148 | Form: STICK
Manufacturer: Conopco Inc. d/b/a Unilever
Category: otc | Type: HUMAN OTC DRUG LABEL
Date: 20101202

ACTIVE INGREDIENTS: Aluminum Zirconium Tetrachlorohydrex GLY 18.2 g/100 g
INACTIVE INGREDIENTS: CYCLOMETHICONE 5; PPG-14 BUTYL ETHER; Stearyl Alcohol; HYDROGENATED CASTOR OIL; TALC; PEG-8 DISTEARATE; BUTYLATED HYDROXYTOLUENE

Suave IS Men Sport antiperspirant deodorant

Active Ingredient

Aluminum Zirconium Tetrachlorohydrex GLY (18.2%)

Purpose
anti-perspirant

Uses
· reduces underarm wetness
· 24 hour protection

Warnings
For External Use Only

Do not use on broken skin

Ask a doctor before use if you have kidney disease

Stop use if rash or irritation occurs

Keep out of reach of children. If swallowed, get medical help or contact a Poison Control Center right away

Directions
· apply to underarms only
· turn dial to raise product

Inactive ingredients
Cyclopentasiloxane
PPG-14 butyl ether
Stearyl Alcohol
Hydrogenated Castor Oil
PEG-8 distearate
Talc
Fragrance (Parfum)
BHT

Questions? Call 1-800-782-8301

PACKAGE LABEL

2.6 oz PDP

PACKAGE LABEL

2.6 oz PDP back